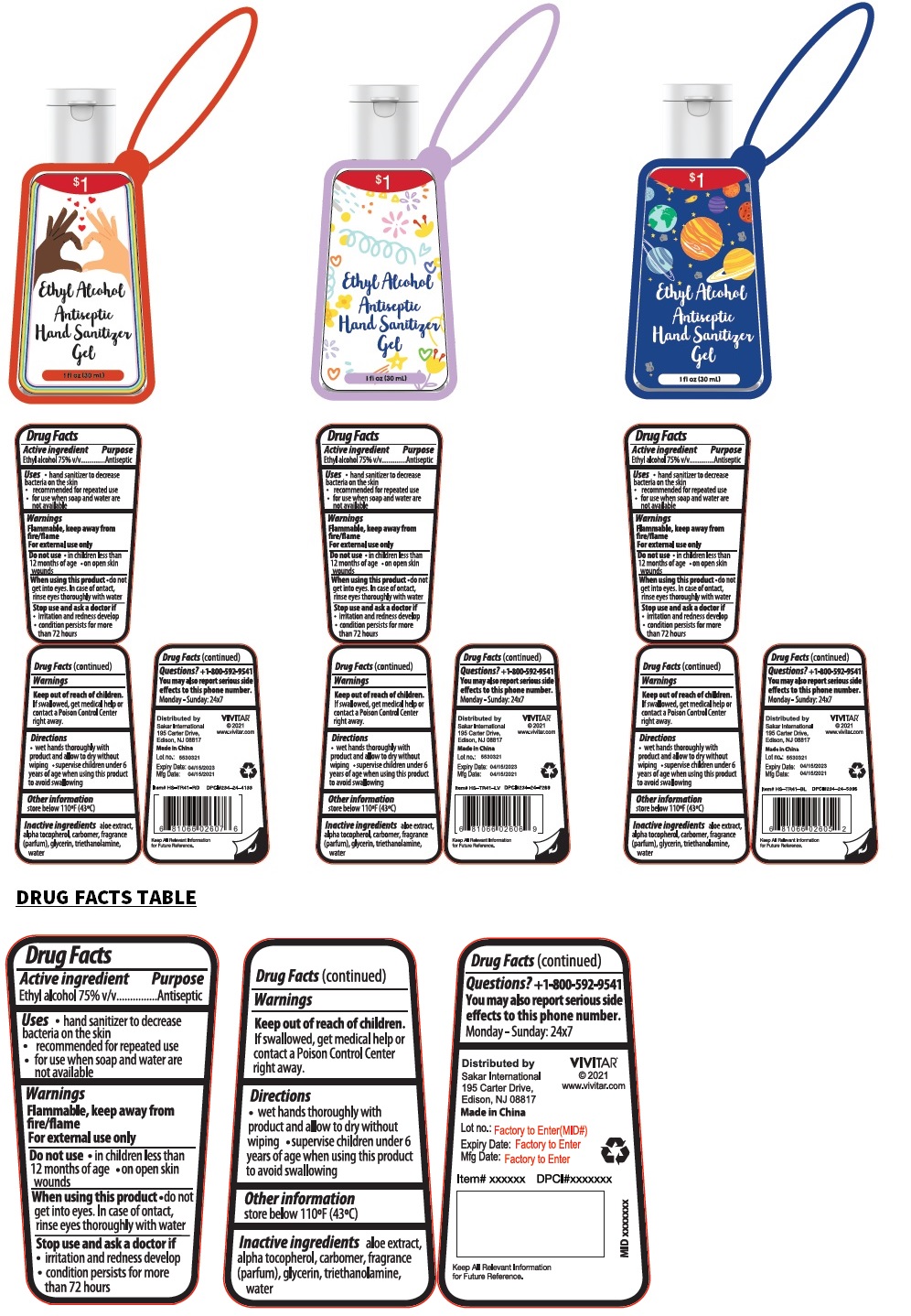 DRUG LABEL: VIVITAR Ethyl Alcohol Antiseptic Hand Sanitizer
NDC: 80800-004 | Form: GEL
Manufacturer: Taizhou Duorui Biotechnology Co., Ltd.
Category: otc | Type: HUMAN OTC DRUG LABEL
Date: 20210426

ACTIVE INGREDIENTS: ALCOHOL 75 mL/100 mL
INACTIVE INGREDIENTS: ALOE; .ALPHA.-TOCOPHEROL; CARBOMER HOMOPOLYMER, UNSPECIFIED TYPE; GLYCERIN; TROLAMINE; WATER

Ethyl Alcohol Antiseptic Hand Sanitizer Gel

Active ingredient

Ethyl alcohol 75% v/v

Purpose

Antiseptic

Uses

• hand sanitizer to decrease bacteria on the skin

• recommended for repeated use

• for use when soap and water are not available

Warnings

Flammable, keep away from fire/flame
For external use only

Do not use

• in children less than 12 months of age • on open skin wounds

When using this product • do not get into eyes. In case of contact, rinse eyes thoroughly with water

Stop use and ask a doctor if

• irritation and redness develop

• condition persists for more than 72 hours

Keep out of reach of children. If swallowed, get medical help or contact a Poison Control Center right away.

Directions

• wet hands thoroughly with product and allow to dry without wiping • supervise children under 6 years of age when using this product to avoid swallowing

Other information

store below 110ºF (43ºC)

Inactive ingredients

aloe extract, alpha tocopherol, carbomer, fragrance (parfum), glycerin, triethanolamine, water

Questions? +1-800-592-9541

You may also report serious side effects to this phone number.
We are available 24x7

Distributed by

Sakar International
195 Carter Drive,
Edison, NJ 08817
www.vivitar.com
Made in China

VIVITAR®

© 2021

Keep All Relevant Information for Future Reference.